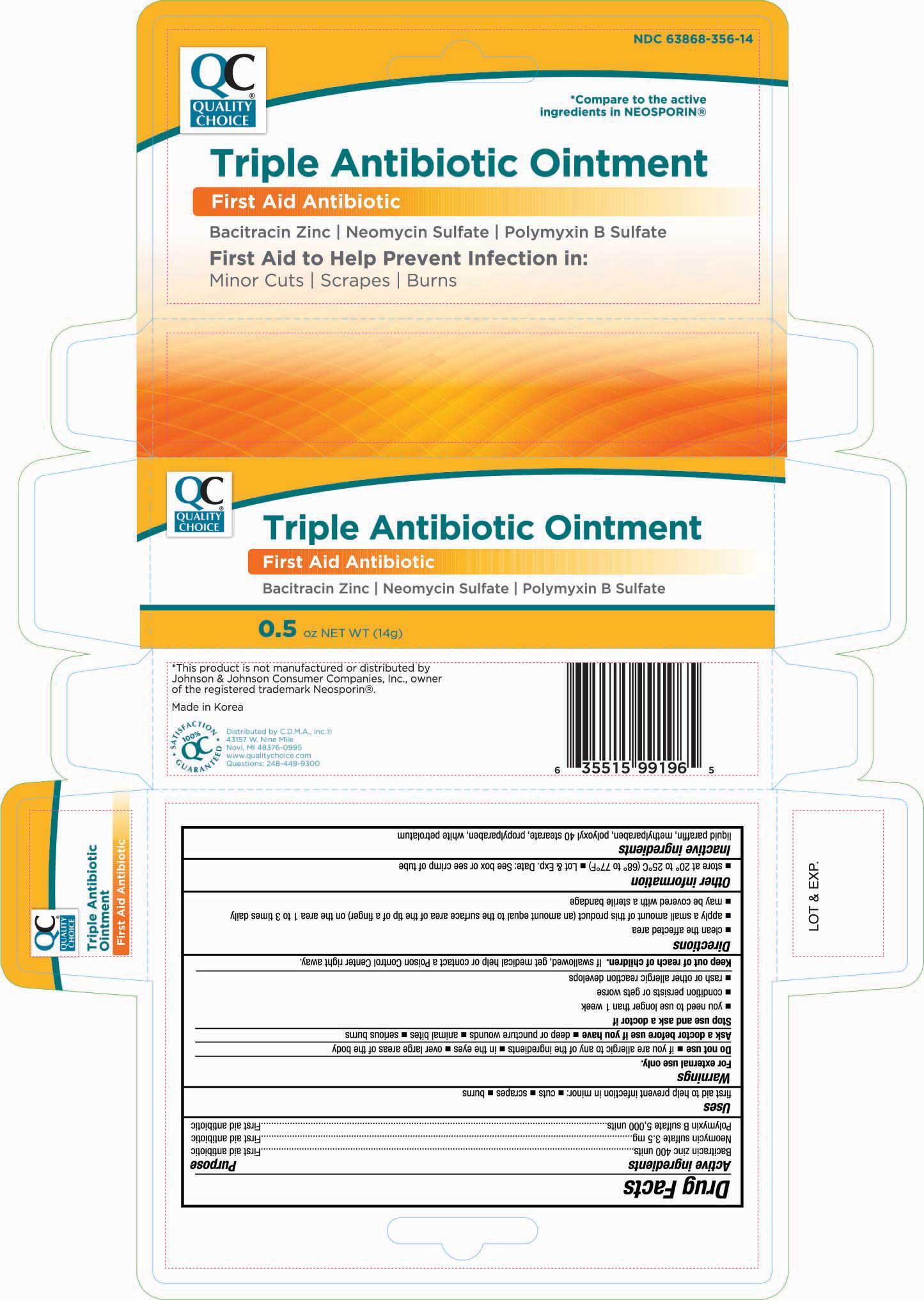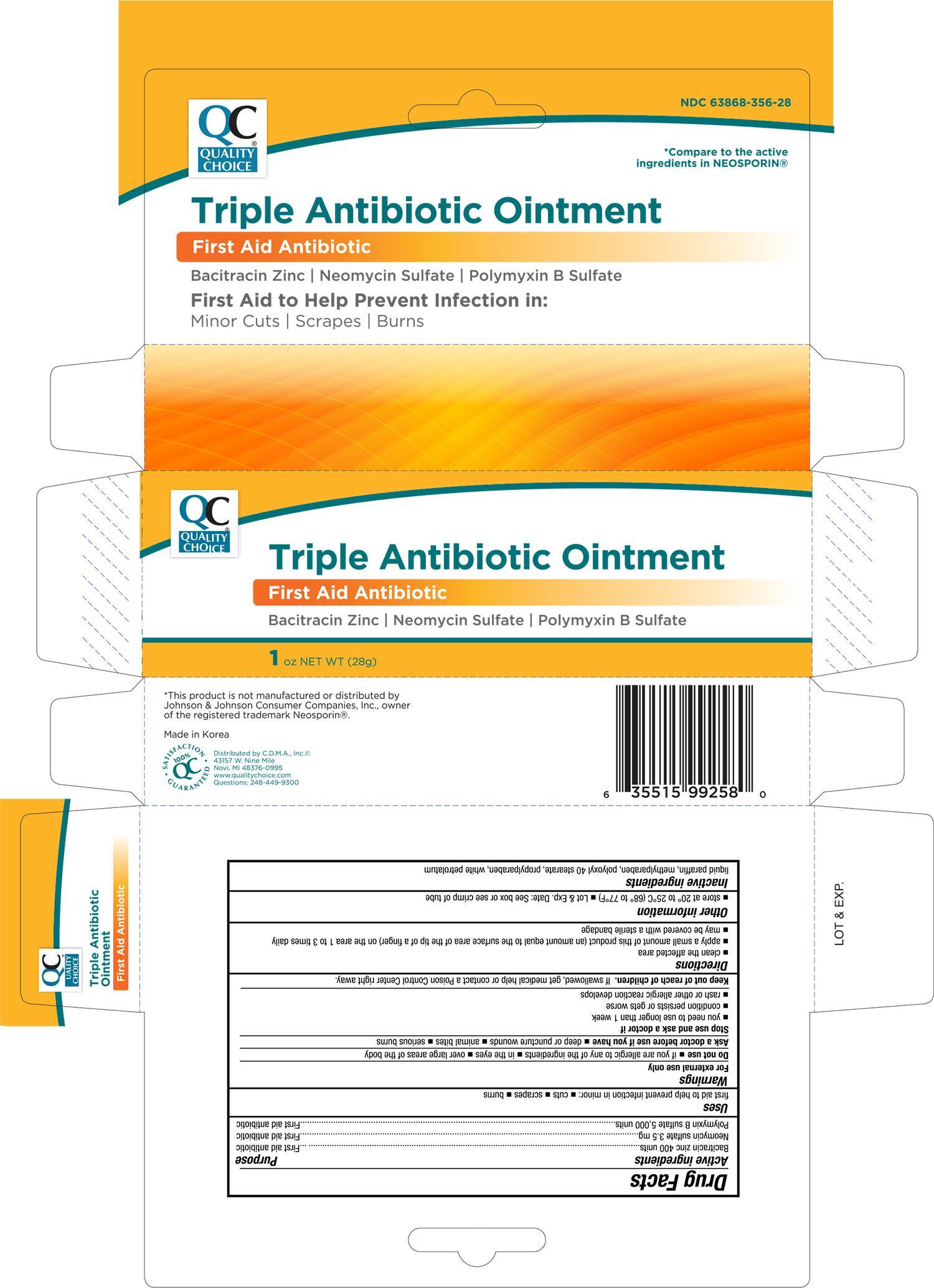 DRUG LABEL: Quality Choice Triple Antibiotic
NDC: 63868-356 | Form: OINTMENT
Manufacturer: Chain Drug Marketing Association Inc
Category: otc | Type: HUMAN OTC DRUG LABEL
Date: 20191205

ACTIVE INGREDIENTS: BACITRACIN ZINC 400 [USP'U]/1 g; NEOMYCIN SULFATE 3.5 mg/1 g; POLYMYXIN B SULFATE 5000 [USP'U]/1 g
INACTIVE INGREDIENTS: PARAFFIN; METHYLPARABEN; POLYOXYL 40 STEARATE; PROPYLPARABEN; PETROLATUM

QC Triple Antibiotic Ointment 0.5 oz 99196, 2019

Active ingredients Purpose

Bacitracin zinc 400 units................................................ First aid antibiotic

Neomycin sulfate 3.5 mg............................................... First aid antibiotic

Polymyxin B sulfate 5,000 units...................................... First aid antibiotic

Uses

first aid to help prevent infection in mirror:

- cuts
- scrapes
- burns

Warnings

For external use only

Do not use

- if you are allergic to any of the ingredients
- in the eyes
- over the large areas of the body

Ask doctor before use if you have

- deep or puncture wounds
- animal bites
- serious burns

Stop use and ask a doctor if

- you need to use longer than 1 week
- condition persists or gets worse
- rash or other allergic reaction develops

Keep out of reach of children. If swallowed, get medical help or contact a Poison Control Center right away.

Directions

- clean the affected area
- apply a small amount of this product (an amount equal to the surface area of the tip of a finger) on the area 1 to 3 times daily
- may be covered with a sterile bandage

Other information

- store at 20° to 25°C (68° to 77°F)
- Lot & Exp. Date: see box or see crimp of tube

Inactive ingredients

liquid paraffin, methylparaben, polyoxyl 40 stearate, propylparaben, white petrolatum

DOSAGE AND ADMINISTRATION

DISTRIBUTED BY:

C.D.M.A., INC.

43157 W. NINE MILE

NOVI, MI 48376-0995

www.qualitychoice.com

MADE IN KOREA